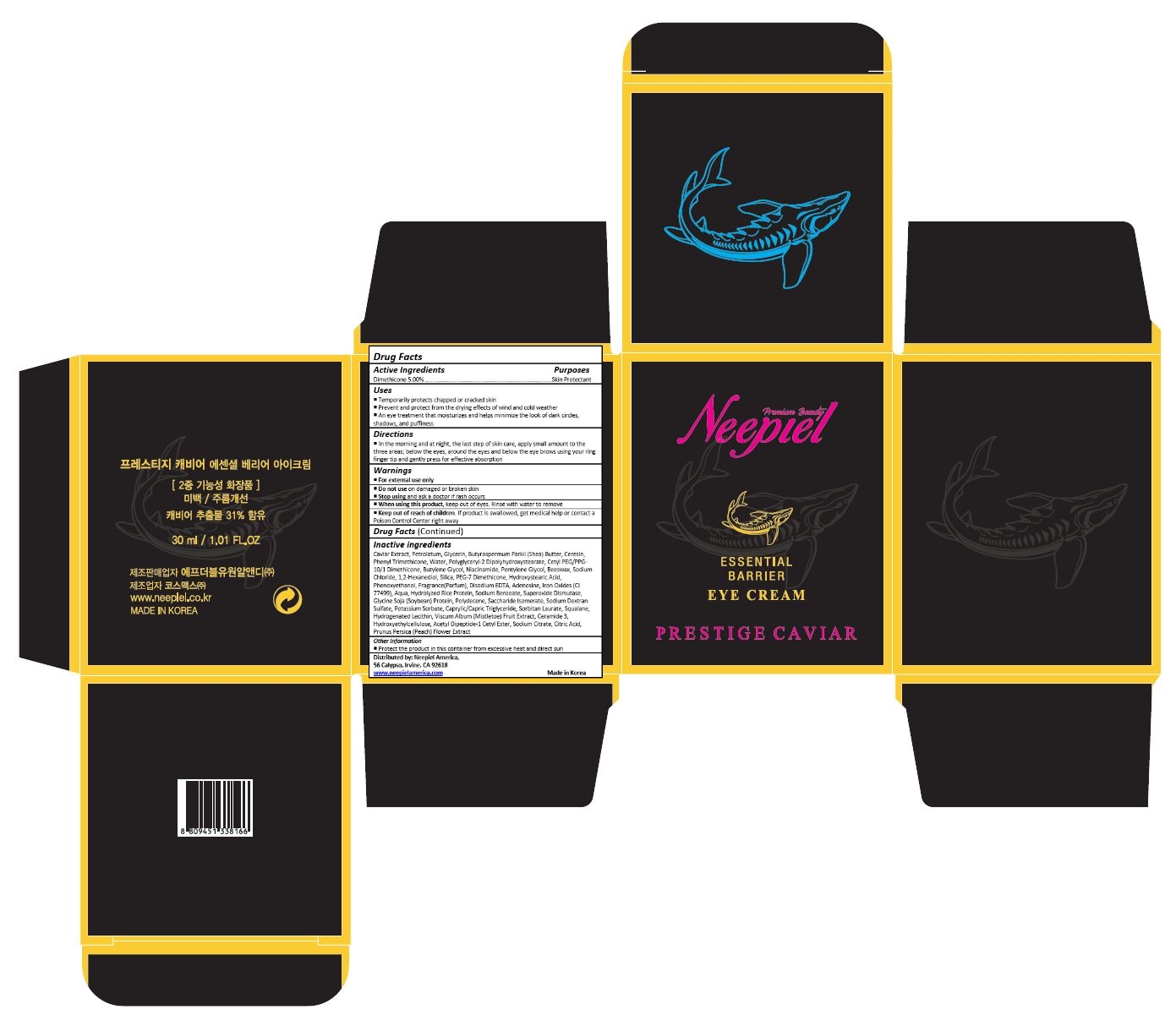 DRUG LABEL: Prestige Caviar Essential Barrier Eye Cream
NDC: 70519-001 | Form: CREAM
Manufacturer: FW1 R&D_Branch
Category: otc | Type: HUMAN OTC DRUG LABEL
Date: 20170627

ACTIVE INGREDIENTS: DIMETHICONE 1.5 mg/30 mL
INACTIVE INGREDIENTS: CAVIAR, UNSPECIFIED; PETROLATUM; GLYCERIN; SHEA BUTTER; CERESIN; PHENYL TRIMETHICONE; WATER; POLYGLYCERYL-2 DIPOLYHYDROXYSTEARATE; CETYL PEG/PPG-10/1 DIMETHICONE (HLB 2); BUTYLENE GLYCOL; NIACINAMIDE; PENTYLENE GLYCOL; YELLOW WAX; SODIUM CHLORIDE; 1,2-HEXANEDIOL; SILICON DIOXIDE; 12-HYDROXYSTEARIC ACID; PHENOXYETHANOL; EDETATE DISODIUM; ADENOSINE; FERROSOFERRIC OXIDE; SODIUM BENZOATE; LEDISMASE; SOY PROTEIN; HYDROGENATED DIDECENE; SACCHARIDE ISOMERATE; POTASSIUM SORBATE; MEDIUM-CHAIN TRIGLYCERIDES; SORBITAN MONOLAURATE; SQUALANE; HYDROGENATED SOYBEAN LECITHIN; VISCUM ALBUM FRUIT; CERAMIDE NP; HYDROXYETHYL CELLULOSE (100 MPA.S AT 2%); ACETYL TYROSYLARGININE CETYL ESTER; SODIUM CITRATE, UNSPECIFIED FORM; CITRIC ACID MONOHYDRATE; PRUNUS PERSICA FLOWER

Drug Facts

ACTIVE INGREDIENT

Dimethicone 5.00%

PURPOSE

Skin Protectant

INDICATIONS AND USAGE

An eye treatment that moisturizes and helps minimize the look of dark circles,
shadows, and puffiness

DOSAGE AND ADMINISTRATION

Apply liberally as needed onto skin

WARNINGS

For external use only.
Do not use on damaged or broken skin.
When using this product, keep out of eyes. Rinse with water to remove
Stop using and ask a doctor if rash occurs.

Keep out of reach of children.

If product is swallowed, get medical help or contact a Poison Control Center right away.

INACTIVE INGREDIENT

Caviar Extract, Petrolatum, Glycerin, Butyrospermum Parkii (Shea) Butter, Ceresin, Phenyl Trimethicone, Water, Polyglyceryl-2 Dipolyhydroxystearate, Cetyl PEG/PPG-10/1 Dimethicone, Butylene Glycol, Niacinamide, Pentylene Glycol, Beeswax, Sodium Chloride, 1,2-Hexanediol, Silica, PEG-7 Dimethicone, Hydroxystearic Acid, Phenoxyethanol, Fragrance(Parfum), Disodium EDTA, Adenosine, Iron Oxides (CI 77499), Aqua, Hydrolyzed Rice Protein, Sodium Benzoate, Superoxide Dismutase, Glycine Soja (Soybean) Protein, Polydecene, Saccharide Isomerate, Sodium Dextran Sulfate, Potassium Sorbate, Caprylic/Capric Triglyceride, Sorbitan Laurate, Squalane, Hydrogenated Lecithin, Viscum Album (Mistletoe) Fruit Extract, Ceramide 3, Hydroxyethylcellulose, Acetyl Dipeptide-1 Cetyl Ester, Sodium Citrate, Citric Acid, Prunus Persica (Peach) Flower Extract